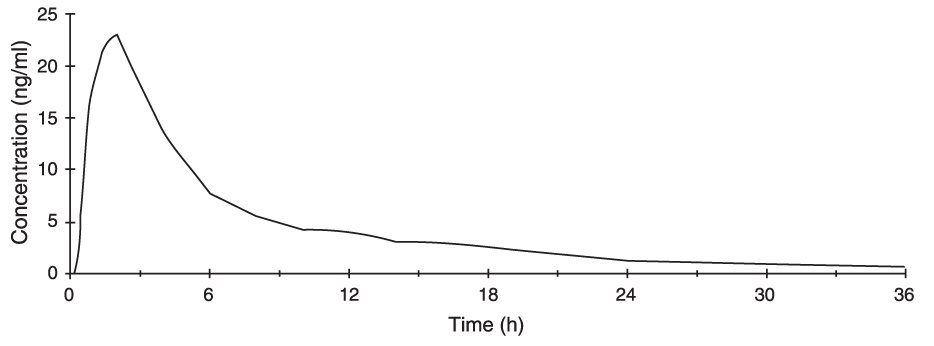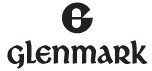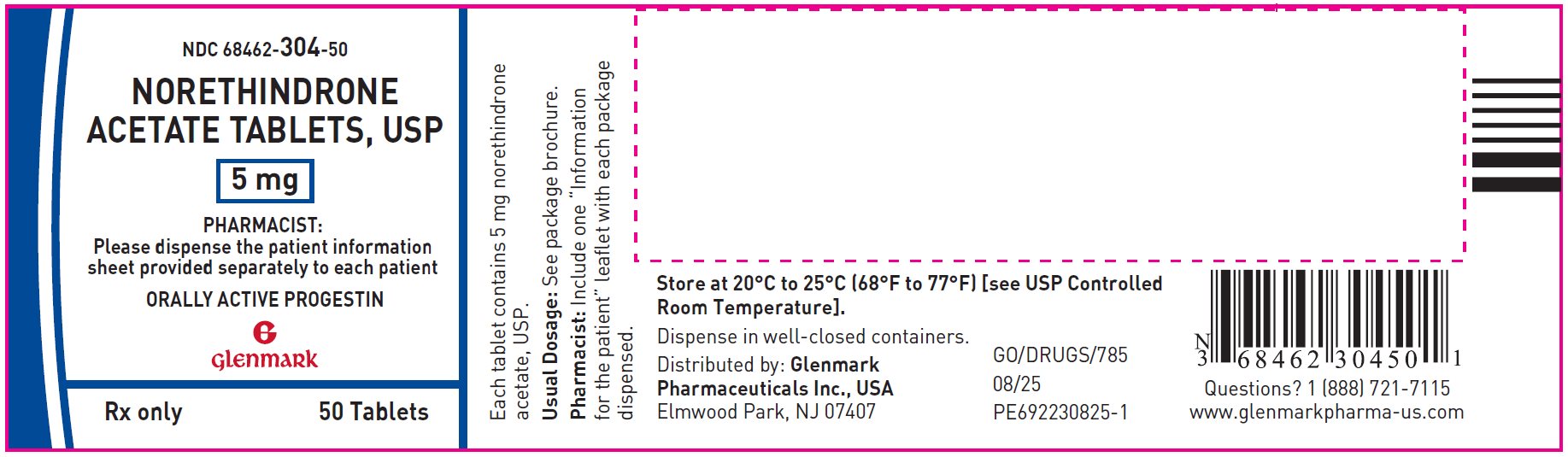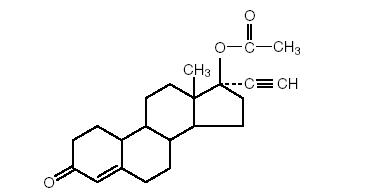 DRUG LABEL: Norethindrone Acetate
NDC: 68462-304 | Form: TABLET
Manufacturer: Glenmark Pharmaceuticals Inc., USA
Category: prescription | Type: HUMAN PRESCRIPTION DRUG LABEL
Date: 20260129

ACTIVE INGREDIENTS: NORETHINDRONE ACETATE 5 mg/1 1
INACTIVE INGREDIENTS: SILICON DIOXIDE; LACTOSE MONOHYDRATE; MAGNESIUM STEARATE; MICROCRYSTALLINE CELLULOSE; TALC

Norethindrone Acetate Tablets USP, 5 mg

DESCRIPTION

Norethindrone acetate tablets USP - 5 mg oral tablets.

Norethindrone acetate USP, (17-hydroxy-19-nor-17α-pregn-4-en-20-yn-3-one acetate), a synthetic, orally active progestin, is the acetic acid ester of norethindrone. It is a white, or creamy white, crystalline powder.

Norethindrone acetate tablets USP, 5 mg contain the following inactive ingredients: colloidal silicon dioxide, lactose monohydrate, magnesium stearate, microcrystalline cellulose and talc.

CLINICAL PHARMACOLOGY

Norethindrone acetate induces secretory changes in an estrogen-primed endometrium. On a weight basis, it is twice as potent as norethindrone.

PHARMACOKINETICS

Absorption:

Norethindrone acetate is completely and rapidly deacetylated to norethindrone (NET) after oral administration, and the disposition of norethindrone acetate is indistinguishable from that of orally administered norethindrone. Norethindrone acetate is rapidly absorbed from norethindrone acetate tablets, with maximum plasma concentration of norethindrone generally occurring at about 2 hours post-dose. The pharmacokinetic parameters of norethindrone following single oral administration of norethindrone acetate in 29 healthy female volunteers are summarized in Table 1.

Table 1 Pharmacokinetic Parameters after a Single Dose of Norethindrone Acetate in Healthy Women
Norethindrone Acetate (n=29) Arithmetic Mean ± SD
Norethindrone (NET)
AUC (0-inf) (ng/ml*h) | 166.90 ± 56.28
Cmax (ng/ml) | 26.19 ± 6.19
tmax (h) | 1.83 ± 0.58
t1/2 (h) | 8.51 ± 2.19
AUC = area under the curve,
Cmax = maximum plasma concentration,
tmax = time at maximum plasma concentration,
t1/2 = half-life,
SD = standard deviation

Figure 1. Mean Plasma Concentration Profile after a Single Dose of 5 mg Administered to 29 Healthy Female Volunteers under Fasting Conditions

Effect of Food:

The effect of food administration on the pharmacokinetics of norethindrone acetate has not been studied.

Distribution:

Norethindrone is 36% bound to sex hormone-binding globulin (SHBG) and 61% bound to albumin. Volume of distribution of norethindrone is about 4 L/kg.

Metabolism:

Norethindrone undergoes extensive biotransformation, primarily via reduction, followed by sulfate and glucuronide conjugation. The majority of metabolites in the circulation are sulfates, with glucuronides accounting for most of the urinary metabolites.

Excretion:

Plasma clearance value for norethindrone is approximately 0.4 L/hr/kg. Norethindrone is excreted in both urine and feces, primarily as metabolites. The mean terminal elimination half-life of norethindrone following a single dose administration of norethindrone acetate is approximately 9 hours.

SPECIAL POPULATIONS

Geriatrics

The effect of age on the pharmacokinetics of norethindrone after norethindrone acetate administration has not been evaluated.

Race

The effect of race on the disposition of norethindrone after norethindrone acetate administration has not been evaluated.

Renal Insufficiency

The effect of renal disease on the disposition of norethindrone after norethindrone acetate administration has not been evaluated. In pre-menopausal women with chronic renal failure undergoing peritoneal dialysis who received multiple doses of an oral contraceptive containing ethinyl estradiol and norethindrone, plasma norethindrone concentration was unchanged compared to concentrations in pre-menopausal women with normal renal function.

Hepatic Insufficiency

The effect of hepatic disease on the disposition of norethindrone after norethindrone acetate administration has not been evaluated. However, norethindrone acetate is contraindicated in markedly impaired liver function or liver disease.

Drug Interactions

No pharmacokinetic drug interaction studies investigating any drug-drug interactions with norethindrone acetate have been conducted.

INDICATIONS AND USAGE

Norethindrone acetate is indicated for the treatment of secondary amenorrhea, endometriosis, and abnormal uterine bleeding due to hormonal imbalance in the absence of organic pathology, such as submucous fibroids or uterine cancer. Norethindrone acetate is not intended, recommended or approved to be used with concomitant estrogen therapy in postmenopausal women for endometrial protection.

CONTRAINDICATIONS

- Known or suspected pregnancy. There is no indication for norethindrone acetate in pregnancy. (See PRECAUTIONS).
- Undiagnosed vaginal bleeding
- Known, suspected or history of cancer of the breast
- Active deep vein thrombosis, pulmonary embolism or history of these conditions
- Active or recent (e.g., within the past year) arterial thromboembolic disease (e.g., stroke, myocardial infarction)
- Impaired liver function or liver disease
- As a diagnostic test for pregnancy
- Hypersensitivity to any of the drug components

WARNINGS

1. Cardiovascular disorders

Patients with risk factors for arterial vascular disease (e.g., hypertension, diabetes mellitus, tobacco use, hypercholesterolemia, and obesity) and/or venous thromboembolism (e.g., personal history or family history of VTE, obesity, and systemic lupus erythematosus) should be managed appropriately.

2. Visual abnormalities

Discontinue medication pending examination if there is a sudden partial or complete loss of vision or if there is sudden onset of proptosis, diplopia, or migraine. If examination reveals papilledema or retinal vascular lesions, medication should be discontinued.

PRECAUTIONS

1. General Precautions

- Because this drug may cause some degree of fluid retention, conditions which might be influenced by this factor, such as epilepsy, migraine, cardiac or renal dysfunctions, require careful observation
- In cases of breakthrough bleeding, and in all cases of irregular bleeding per vagina, nonfunctional causes should be borne in mind. In cases of undiagnosed vaginal bleeding, adequate diagnostic measures are indicated
- Patients who have a history of clinical depression should be carefully observed and the drug discontinued if the depression recurs to a serious degree
- Data suggest that progestin therapy may have adverse effects on lipid and carbohydrate metabolism. The choice of progestin, its dose, and its regimen may be important in minimizing these adverse effects, but these issues will require further study before they are clarified. Women with hyperlipidemias and/or diabetes should be monitored closely during progestin therapy
- The pathologist should be advised of progestin therapy when relevant specimens are submitted

2. Information for the Patient

Healthcare providers are advised to discuss the PATIENT INFORMATION leaflet with patients for whom they prescribe norethindrone acetate.

3. Drug/Laboratory Tests Interactions

The following laboratory test results may be altered by the use of estrogen/progestin combination drugs:

- Accelerated prothrombin time, partial thromboplastin time, and platelet aggregation time; increased platelet count; increased factors II, VII antigen, VIII antigen, VIII coagulant activity, IX, X, XII, VII-X complex, II-VII-X complex, and beta-thromboglobulin; decreased levels of antifactor Xa and antithrombin III, decreased antithrombin III activity; increased levels of fibrinogen and fibrinogen activity; increased plasminogen antigen and activity.
- Increased thyroid-binding globulin (TBG) levels leading to increased circulating total thyroid hormone levels as measured by protein-bound iodine (PBI), T4 levels (by column or by radioimmunoassay) or T3 levels by radio immunoassay. T3 resin uptake is decreased, reflecting the elevated TBG. Free T4 and free T3 concentrations are unaltered. Patients on thyroid replacement therapy may require higher doses of thyroid hormone.
- Other binding proteins may be elevated in serum (i.e., corticosteroid binding globulin (CBG), sex hormone binding globulin (SHBG)) leading to increased circulating corticosteroid and sex steroids, respectively. Free or biologically active hormone concentrations are unchanged. Other plasma proteins may be increased (angiotensinogen/renin substrate, alpha-1-antitrypsin, ceruloplasmin).
- Increased plasma HDL and HDL2 cholesterol subfraction concentrations, reduced LDL cholesterol concentration, increased triglycerides levels.
- Impaired glucose metabolism.
- Reduced response to metyrapone test.

4. Carcinogenesis, Mutagenesis, and Impairment of Fertility

Some beagle dogs treated with medroxyprogesterone acetate developed mammary nodules. Although nodules occasionally appeared in control animals, they were intermittent in nature, whereas nodules in treated animals were larger and more numerous, and persisted. There is no general agreement as to whether the nodules are benign or malignant. Their significance with respect to humans has not been established.

5. Pregnancy Category X

Norethindrone acetate is contraindicated during pregnancy as it may cause fetal harm when administered to pregnant women. Several reports suggest an association between intrauterine exposure to progestational drugs in the first trimester of pregnancy and congenital abnormalities in male and female fetuses. Some progestational drugs induce mild virilization of the external genitalia of female fetuses.

6. Nursing Mothers

Detectable amounts of progestins have been identified in the milk of mothers receiving them. Caution should be exercised when progestins are administered to a nursing woman.

7. Pediatric Use

Norethindrone acetate tablets are not indicated in children.

ADVERSE REACTIONS

See WARNINGS and PRECAUTIONS. The following adverse reactions have been observed in women taking progestins:

- Breakthrough bleeding
- Spotting
- Change in menstrual flow
- Amenorrhea
- Edema
- Changes in weight (decreases, increases)
- Changes in the cervical squamo-columnar junction and cervical secretions
- Cholestatic jaundice
- Rash (allergic) with and without pruritus
- Melasma or chloasma
- Clinical depression
- Acne
- Breast enlargement/tenderness
- Headache/migraine
- Urticaria
- Abnormalities of liver tests (i.e., AST, ALT, Bilirubin)
- Decreased HDL cholesterol and increased LDL/HDL ratio
- Mood swings
- Nausea
- Insomnia
- Anaphylactic/anaphylactoid reactions
- Thrombotic and thromboembolic events (e.g., deep vein thrombosis, pulmonary embolism, retinal vascular thrombosis, cerebral thrombosis and embolism)
- Optic neuritis (which may lead to partial or complete loss of vision)

DOSAGE AND ADMINISTRATION

Therapy with norethindrone acetate must be adapted to the specific indications and therapeutic response of the individual patient.

Secondary amenorrhea, abnormal uterine bleeding due to hormonal imbalance in the absence of organic pathology:

2.5 to 10 mg norethindrone acetate may be given daily for 5 to 10 days to produce secretory transformation of an endometrium that has been adequately primed with either endogenous or exogenous estrogen.

Progestin withdrawal bleeding usually occurs within three to seven days after discontinuing norethindrone acetate therapy. Patients with a past history of recurrent episodes of abnormal uterine bleeding may benefit from planned menstrual cycling with norethindrone acetate.

Endometriosis:

Initial daily dosage of 5 mg norethindrone acetate for two weeks. Dosage should be increased by 2.5 mg per day every two weeks until 15 mg per day of norethindrone acetate is reached. Therapy may be held at this level for six to nine months or until annoying breakthrough bleeding demands temporary termination.

HOW SUPPLIED

Norethindrone acetate tablets USP are available as:

5 mg: White to off-white oval, flat faced beveled edged, uncoated tablets debossed with ‘G with breakline’ on one side and 304 on other side.

Available as follows:

Bottles of 50 NDC 68462-304-50
Bottles of 500 NDC 68462-304-05

STORAGE AND HANDLING

Store at 20° to 25°C (68° to 77°F) [See USP Controlled Room Temperature].

Distributed by:

Glenmark Pharmaceuticals Inc., USA
Elmwood Park, NJ 07407

Questions? 1 (888)721-7115
www.glenmarkpharma-us.com

August 2025

PATIENT INFORMATION

Norethindrone acetate tablets USP, 5 mg

Read this PATIENT INFORMATION before you start taking norethindrone acetate tablets and read what you get each time you refill norethindrone acetate tablets. There may be new information. This information does not take the place of talking to your healthcare provider about your medical condition.

What is the most important information I should know about norethindrone acetate (A Progestin Hormone) tablets?

- Do not use norethindrone acetate if you are pregnant, breastfeeding or are trying to conceive.
- Do not use northindrone acetate if you have had a previous blood clot, stroke, or heart attack.
- Do not use norethindrone acetate if you are postmenopausal.

What is norethindrone acetate?

Norethindrone acetate is similar to the progesterone hormones naturally produced by the body. Your healthcare provider may provide norethindrone acetate as individual tablets.

What are norethindrone acetate tablets used for?

Norethindrone acetate tablets are used for the treatment of secondary amenorrhea (absence of menstrual periods in women who have previously had a menstrual period who are not pregnant), the treatment of endometriosis, and the treatment of irregular menstrual periods due to hormone imbalance.

Who should not take norethindrone acetate tablets?

You should not take norethindrone acetate tablets if you are postmenopausal, pregnant or breastfeeding.

You should not take norethindrone acetate tablets if you have the following conditions:

- Known or suspected pregnancy. Norethindrone acetate tablets are not indicated during pregnancy as it may cause fetal harm when administered to pregnant women. There is an increased risk of minor birth defects in children whose mothers take norethindrone acetate during the first 4 months of pregnancy (mild masculinization of the external genitalia of the female fetus, as well as hypospadias in the male fetus). If you take norethindrone acetate and later find out you were pregnant, talk with your healthcare provider right away
- History of blood clots in the legs, lungs, eyes, brain, or elsewhere, or a past history of these conditions
- Liver impairment or disease
- Known or suspected cancer of the breast. If you have or had cancer of the breast, talk with your healthcare provider about whether you should take norethindrone acetate
- Undiagnosed vaginal bleeding
- Hypersensitivity to norethindrone acetate tablets. See the end of this leaflet for a list of all of the ingredients in norethindrone acetate

What are the risks associated with norethindrone acetate tablets?

- Risk to the Fetus:
  Norethindrone acetate tablets should not be used if you are pregnant. Norethindrone acetate tablets are contraindicated during pregnancy as it may cause fetal harm when administered to pregnant women. There is an increased risk of minor birth defects in children whose mothers take this drug during the first 4 months of pregnancy. Several reports suggest an association between mothers who take these drugs in the first trimester of pregnancy and congenital abnormalities in male and female babies. Although it is not clear that these events were drug related, you should check with your healthcare provider about the risks to your unborn child of any medication taken during pregnancy.
  You should avoid using norethindrone acetate tablets during pregnancy. If you take norethindrone acetate tablets and later find you were pregnant when you took it, be sure to discuss this with your healthcare provider as soon as possible.
- Abnormal Blood Clotting:
  Use of progestational drugs, such as norethindrone acetate, has been associated with changes in the blood-clotting system. These changes allow the blood to clot more easily, possibly allowing clots to form in the bloodstream. If blood clots do form in your bloodstream, they can cut off the blood supply to vital organs, causing serious problems. These problems may include a stroke (by cutting off blood to part of the brain), a heart attack (by cutting off blood to part of the heart), a pulmonary embolus (by cutting off blood to part of the lungs), visual loss or blindness (by cutting off blood vessels in the eye), or other problems. Any of these conditions may cause death or serious long-term disability. Call your healthcare provider right away if you suspect you have any of these conditions. He or she may advise you to stop using the drug.
- Eye Abnormalities:
  Discontinue norethindrone acetate tablets and call your healthcare provider right away if you experience sudden partial or complete loss of vision, blurred vision, or sudden onset of bulging eyes, double vision, or migraine.

These are some of the warning signs of serious side effects with progestin therapy:

- Breast lumps
- Dizziness and faintness
- Changes in speech
- Severe headaches
- Chest pain
- Shortness of breath
- Pain in your legs
- Changes in vision

Call your healthcare provider right away if you get any of these warning signs, or any other unusual symptom that concerns you.

Common side effects include:

- Headache
- Breast pain
- Irregular vaginal bleeding or spotting
- Stomach/abdominal cramps/bloating
- Nausea and vomiting
- Hair loss

Other side effects include:

- High blood pressure
- Liver problems
- High blood sugar
- Fluid retention
- Enlargements of benign tumors of the uterus ("fibroids")
- Vaginal yeast infections
- Mental depression

These are not all the possible side effects of progestin and/or estrogen therapy. For more information, ask your healthcare provider or pharmacist.

What can I do to lower my chances of getting a serious side effect with norethindrone acetate?

- Talk with your healthcare provider regularly about whether you should continue taking norethindrone acetate
- Have a breast exam and mammogram (breast x-ray) every year unless your healthcare provider tells you something else. If members of your family have had breast cancer or if you have ever had breast lumps or an abnormal mammogram, you may need to have breast exams more often
- If you have high blood pressure, high cholesterol (fat in the blood), diabetes, are overweight, or if you use tobacco, you may have higher chances for getting heart disease. Ask your healthcare provider for ways to lower your chances of getting heart attacks

General information about the safe and effective use of norethindrone acetate tablets

Medicines are sometimes prescribed for conditions that are not mentioned in patient information leaflets. Do not take norethindrone acetate tablets for conditions for which it was not prescribed. Do not give norethindrone acetate tablets to other people, even if they have the same symptoms you have. It may harm them.

Keep norethindrone acetate tablets out of the reach of children.

This leaflet provides a summary of the most important information about progestin and/or estrogen therapy. If you would like more information, talk with your healthcare provider or pharmacist. You can ask for information about norethindrone acetate that is written for health professionals.

What are the ingredients in norethindrone acetate tablets?

Norethindrone acetate tablets contain the following inactive ingredients: colloidal silicon dioxide, lactose monohydrate, magnesium stearate, microcrystalline cellulose and talc.

Distributed by:

Glenmark Pharmaceuticals Inc., USA
Elmwood Park, NJ 07407

Questions? 1 (888)721-7115
www.glenmarkpharma-us.com

Revised: August 2025

Principal Display Panel

NDC 68462-304-50

Norethindrone Acetate Tablets USP

Bottle Label

5 mg 50 tablets